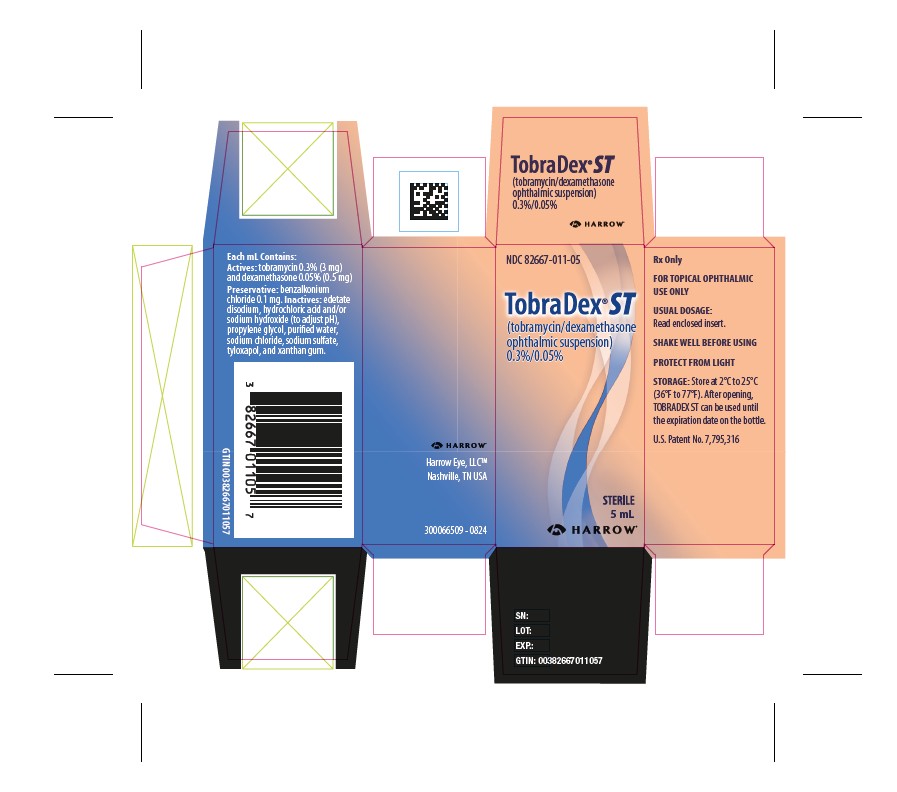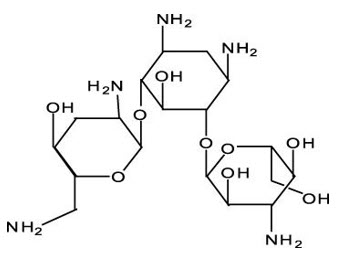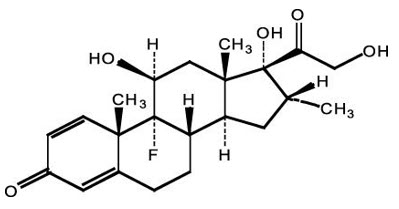 DRUG LABEL: Tobradex ST
NDC: 82667-011 | Form: SUSPENSION/ DROPS
Manufacturer: Harrow Eye, LLC
Category: prescription | Type: HUMAN PRESCRIPTION DRUG LABEL
Date: 20250401

ACTIVE INGREDIENTS: TOBRAMYCIN 3 mg/1 mL; DEXAMETHASONE 0.5 mg/1 mL
INACTIVE INGREDIENTS: BENZALKONIUM CHLORIDE; XANTHAN GUM; TYLOXAPOL; EDETATE DISODIUM; SODIUM CHLORIDE; PROPYLENE GLYCOL; SODIUM SULFATE; HYDROCHLORIC ACID; SODIUM HYDROXIDE; WATER

HIGHLIGHTS OF PRESCRIBING INFORMATION

These highlights do not include all the information needed to use TOBRADEX ST safely and effectively. See full prescribing information for TOBRADEX ST.
TOBRADEX®ST (tobramycin and dexamethasone ophthalmic suspension) 0.3%/0.05%, for topical ophthalmic use
Initial U.S. Approval: 1988

1 INDICATIONS AND USAGE

TOBRADEX ST is a topical antibiotic and corticosteroid combination for steroid-responsive inflammatory ocular conditions for which a corticosteroid is indicated and where superficial bacterial ocular infection or a risk of bacterial ocular infection exists. (1).

2 DOSAGE AND ADMINISTRATION

- Instill one drop into the conjunctival sac(s) every 4 to 6 hours. (2.1)
- During the initial 24 to 48 hours, dosage may be increased to one drop every 2 hours. (2.1)
- Frequency should be decreased gradually as warranted by improvement in clinical signs, but care should be taken not to discontinue therapy prematurely. (2.1)

3 DOSAGE FORMS AND STRENGTHS

TOBRADEX ST ophthalmic suspension contains 0.3% (3 mg/mL) tobramycin and 0.05% (0.5 mg/mL) dexamethasone. (3)

4 CONTRAINDICATIONS

- TOBRADEX ST, as with other ophthalmic corticosteroids, is contraindicated in most viral diseases of the cornea and conjunctiva, including epithelial herpes simplex keratitis (dendritic keratitis), vaccinia, and varicella, and also in mycobacterial infection of the eye and fungal diseases of ocular structures. (4.1)
- Hypersensitivity to any component of the medication (4.2)

5 WARNINGS AND PRECAUTIONS

- Intraocular Pressure (IOP) Increase: Prolonged use of corticosteroids may result in glaucoma with damage to the optic nerve, defects in visual acuity and fields of vision. If this product is used for 10 days or longer, IOP should be monitored. (5.1).
- Sensitivity to topically applied aminoglycosides may occur. (5.2)
- Cataracts: Use of corticosteroids may result in posterior subcapsular cataract formation. (5.3)
- Delayed Healing: The use of steroids after cataract surgery may delay healing and increase the incidence of bleb formation. In those diseases causing thinning of the cornea or sclera, perforations have been known to occur with the use of topical steroids. The initial prescription and renewal of the medication order should be made by a physician only after examination of the patient with the aid of magnification such as slit lamp biomicroscopy and, where appropriate, fluorescein staining. (5.4)
- Bacterial Infections: Prolonged use of corticosteroids may suppress the host response and thus increase the hazard of secondary ocular infections. In acute purulent conditions, steroids may mask infection or enhance existing infection. If signs and symptoms fail to improve after 2 days, the patient should be re-evaluated. (5.5)
- Viral Infections: Employment of a corticosteroid medication in the treatment of patients with a history of herpes simplex requires great caution. Use of ocular steroids may prolong the course and may exacerbate the severity of many viral infections of the eye (including herpes simplex). (5.6)
- Fungal Infections: Fungal infections of the cornea are particularly prone to develop coincidentally with long-term local steroid application. Fungus invasion must be considered in any persistent corneal ulceration where a steroid has been used or is in use. (5.7)
- Vision Blurred: Vision may be temporarily blurred following dosing with TOBRADEX ST. Care should be exercised in operating machinery or driving a motor vehicle. (5.8)

6 ADVERSE REACTIONS

Most common adverse reactions to topical ocular tobramycin are hypersensitivity and localized ocular toxicity, including eye pain, eyelids pruritus, eyelid edema, and conjunctival hyperemia. The reactions due to the steroid component are increases in IOP with possible development of glaucoma. (6)

To report SUSPECTED ADVERSE REACTIONS, contact Harrow at 1-833-4HARROW(427769) or FDA at 1-800-FDA-1088 or www.fda.gov/medwatch.

FULL PRESCRIBING INFORMATION

1 INDICATIONS AND USAGE

TOBRADEX ST ophthalmic suspension is indicated for steroid-responsive inflammatory ocular conditions for which a corticosteroid is indicated and where superficial bacterial ocular infection or a risk of bacterial ocular infection exists.

Ocular steroids are indicated in inflammatory conditions of the palpebral and bulbar conjunctiva, cornea and anterior segment of the globe where the inherent risk of steroid use in certain infective conjunctivitides is accepted to obtain a diminution in edema and inflammation. They are also indicated in chronic anterior uveitis and corneal injury from chemical, radiation or thermal burns, or penetration of foreign bodies.

The use of a combination drug with an anti-infective component is indicated where the risk of superficial ocular infection is high or where there is an expectation that potentially dangerous numbers of bacteria will be present in the eye.

The particular anti-infective drug in this product is active against the following common bacterial eye pathogens: Staphylococci, including S. aureusand S. epidermidis (coagulase-positive and coagulase-negative), including penicillin-resistant isolates. Streptococci, including some Group A and other beta-hemolytic species, some nonhemolytic species, and some Streptococcus pneumoniae, Pseudomonas aeruginosa, Escherichia coli, Klebsiella pneumoniae, Enterobacter aerogenes, Proteus mirabilis, Morganella morganii, most Proteus vulgaris isolates, Haemophilus influenzae, H. aegyptius, Moraxella lacunata, Acinetobacter calcoaceticus, and some Neisseria species.

2 DOSAGE AND ADMINISTRATION

2.1 Initiation and Continuation of Treatment

Evaluate intraocular pressure (IOP) prior to the initial prescription and renewal of the medication order [see Warnings and Precautions (5.1)] .

Perform ophthalmic examination with the aid of magnification, such as slit lamp biomicroscopy, and, where appropriate, fluorescein staining, prior to the initial prescription and renewal of the medication order. Re-evaluate the patient if signs and symptoms fail to improve after 2 days [see Warnings and Precautions (5.4, 5.5)] .

Not more than one bottle should be prescribed initially, and the prescription should not be refilled without further evaluation.

2.2 Recommended Dosage

Instill one drop into the conjunctival sac(s) every 4 to 6 hours. During the initial 24 to 48 hours, the dosage may be increased to one drop every 2 hours. Frequency should be decreased gradually as warranted by improvement in clinical signs. Care should be taken not to discontinue therapy prematurely. Shake well before use.

3 DOSAGE FORMS AND STRENGTHS

TOBRADEX ST ophthalmic suspension 0.3%/0.05% contains 3 mg/mL tobramycin and 0.5 mg/mL dexamethasone.

4 CONTRAINDICATIONS

4.1 Nonbacterial Etiology

TOBRADEX ST, as with other ophthalmic corticosteroids, is contraindicated in most viral diseases of the cornea and conjunctiva, including epithelial herpes simplex keratitis (dendritic keratitis), vaccinia, and varicella, and also in mycobacterial infection of the eye and fungal diseases of ocular structures.

4.2 Hypersensitivity

Hypersensitivity to a component of the medication.

5 WARNINGS AND PRECAUTIONS

5.1 Intraocular Pressure Increase

Prolonged use of corticosteroids may result in glaucoma with damage to the optic nerve, defects in visual acuity and fields of vision. If this product is used for 10 days or longer, intraocular pressure (IOP) should be monitored.

5.2 Aminoglycoside Sensitivity

Sensitivity to topically applied aminoglycosides may occur.

5.3 Cataracts

Use of corticosteroids may result in posterior subcapsular cataract formation.

5.4 Delayed Healing

The use of steroids after cataract surgery may delay healing and increase the incidence of bleb formation. In those diseases causing thinning of the cornea or sclera, perforations have been known to occur with the use of topical steroids. The initial prescription and renewal of the medication order should be made by a physician only after examination of the patient with the aid of magnification such as slit lamp biomicroscopy and, where appropriate, fluorescein staining.

5.5 Bacterial Infections

Prolonged use of corticosteroids may suppress the host response and thus increase the hazard of secondary ocular infections. In acute purulent conditions, steroids may mask infection or enhance existing infection. If signs and symptoms fail to improve after 2 days, the patient should be reevaluated.

5.6 Viral Infections

Employment of a corticosteroid medication in the treatment of patients with a history of herpes simplex requires great caution. Use of ocular steroids may prolong the course and may exacerbate the severity of many viral infections of the eye (including herpes simplex).

5.7 Fungal Infections

Fungal infections of the cornea are particularly prone to develop coincidentally with long-term local steroid application. Fungus invasion must be considered in any persistent corneal ulceration where a steroid has been used or is in use.

5.8 Vision Blurred

Vision may be temporarily blurred following dosing with TOBRADEX ST. Care should be exercised in operating machinery or driving a motor vehicle.

5.9 Risk of Contamination

Do not touch the dropper tip of the bottle to any surface, as this may contaminate the contents.

5.10 Contact Lens Use

TOBRADEX ST contains benzalkonium chloride, an antimicrobial preservative, that may be absorbed by soft contact lenses. Contact lenses should not be worn during the use of TOBRADEX ST.

6 ADVERSE REACTIONS

6.1 Clinical Trials Experience

Because clinical trials are conducted under widely varying conditions, adverse reaction rates observed in the clinical trials of a drug cannot be directly compared to rates in the clinical trials of another drug and may not reflect the rates observed in practice.

Adverse reactions have occurred with steroid/anti-infective combination drugs, which can be attributed to the steroid component, the anti-infective component, or the combination. Exact incidence figures are not available.

The most frequent adverse reactions to topical ocular tobramycin (TOBREX®) are hypersensitivity and localized ocular toxicity, including eye pain, eyelids pruritus, eyelid edema, and conjunctival hyperemia. These reactions occur in less than 4% of patients.

The reactions due to the steroid component are: increased IOP with possible development of glaucoma, and infrequent optic nerve disorder; subcapsular cataract; and impaired healing [see Warnings and Precautions (5.1, 5.3, 5.4)] .

The development of secondary infection has occurred after use of combinations containing steroids and antimicrobials. Fungal infections of the cornea are particularly prone to develop coincidentally with long-term applications of steroids [see Warnings and Precautions (5.7)] . The possibility of fungal invasion must be considered in any persistent corneal ulceration where steroid treatment has been used. Secondary bacterial ocular infection following suppression of host responses also occurs.

Non-ocular adverse events occurring at an incidence of 0.5% to 1% included headache and increased blood pressure.

The following additional adverse reactions have been reported with the individual components below:

Aminoglycosides: Neurotoxicity, ototoxicity, and nephrotoxicity have occurred in patients receiving systemic aminoglycoside therapy. Aminoglycosides may aggravate muscle weakness in patients with known or suspected neuromuscular disorders, such as myasthenia gravis or Parkinson's disease, because of their potential effect on neuromuscular function.

Dexamethasone: Cushing's syndrome and adrenal suppression may occur after use of dexamethasone in excess of the listed dosing instructions in predisposed patients, including children and patients treated with CYP3A4 inhibitors.

6.2 Postmarketing Experience

The following adverse reactions have been identified during postapproval use of TOBRADEX ST. Because these reactions are reported voluntarily from a population of uncertain size, it is not always possible to reliably estimate their frequency or establish a causal relationship to drug exposure.

Additional adverse reactions identified from postapproval use include, anaphylactic reaction, and erythema multiforme.

8 USE IN SPECIFIC POPULATIONS

8.1 Pregnancy

Corticosteroids have been shown to be teratogenic in animal studies. Ocular administration of 0.1% dexamethasone resulted in 15.6% and 32.3% incidence of fetal anomalies in 2 groups of pregnant rabbits. Fetal growth retardation and increased mortality rates have been observed in rats with chronic dexamethasone therapy. Reproduction studies have been performed in rats and rabbits with tobramycin at doses up to 100 mg/kg/day (equivalent to human doses of 16 and 32 mg/kg/day, respectively) and have revealed no evidence of impaired fertility or harm to the fetus.

There are no adequate and well-controlled studies in pregnant women. However, prolonged or repeated corticoid use during pregnancy has been associated with an increased risk of intra-uterine growth retardation. Infants born of mothers who have received substantial doses of corticosteroids during pregnancy should be observed carefully for signs of hypoadrenalism. TOBRADEX ST ophthalmic suspension should be used during pregnancy only if the potential benefit justifies the potential risk to the fetus [see Nonclinical Toxicology (13.1)] .

8.3 Nursing Mothers

Systemically administered corticosteroids appear in human milk and could suppress growth, interfere with endogenous corticosteroid production, or cause other untoward effects. It is not known whether topical administration of corticosteroids could result in sufficient systemic absorption to produce detectable quantities in human milk. Because many drugs are excreted in human milk, caution should be exercised when TOBRADEX ST is administered to a nursing woman.

8.4 Pediatric Use

Safety and effectiveness in pediatric patients below the age of 2 years have not been established.

8.5 Geriatric Use

No overall differences in safety or effectiveness have been observed between elderly and younger patients.

11 DESCRIPTION

TOBRADEX ST (tobramycin and dexamethasone ophthalmic suspension) 0.3%/0.05% is a sterile, isotonic, white, aqueous antibiotic and steroid suspension with a pH of approximately 5.7 and an osmolality of approximately 290 mOsm/kg.

The chemical name of tobramycin is O-3-amino-3-deoxy-α-D-glucopyranosyl-(1→4)-O-[2,6-diamino- 2,3,6-trideoxy-α-D-ribo-hexopyranosyl-(1→6)]-2-deoxy- L-streptamine. It has a molecular formula of C18H37N5O9and a molecular weight of 467.52 g/mol. The chemical structure is:

The chemical name of dexamethasone is 9-fluoro-11β,17,21-trihydroxy-16α-methylpregna-1,4-diene-3,20-dione. It has a molecular formula of C22H29FO5and a molecular weight of 392.47 g/mol. The chemical structure is:

Each mL of TOBRADEX ST contains: Actives:tobramycin 3 mg and dexamethasone 0.5 mg. Preservative:benzalkonium chloride 0.1 mg. Inactives:edetate disodium, hydrochloric acid and/or sodium hydroxide (to adjust pH), propylene glycol, purified water, sodium chloride, sodium sulfate, tyloxapol, and xanthan gum.

12 CLINICAL PHARMACOLOGY

12.1 Mechanism of Action

Dexamethasone is a potent corticoid. Corticoids suppress the inflammatory response to a variety of agents and they can delay or slow healing. Since corticoids may inhibit the body's defense mechanism against infection, a concomitant antimicrobial drug may be used when this inhibition is considered to be clinically significant.

Tobramycin is an antibacterial drug. It inhibits the growth of bacteria by inhibiting protein synthesis. Tobramycin is included in this combination product to provide action against susceptible bacteria [see Microbiology (12.4)] .

12.3 Pharmacokinetics

In a multi-center, double-masked, parallel-group, randomized, single-dose pharmacokinetic study in male and female cataract surgery patients, mean dexamethasone concentrations following administration of TOBRADEX ST were similar to dexamethasone concentrations following administration of TOBRADEX (tobramycin and dexamethasone ophthalmic suspension) 0.3%/0.1%. Aqueous humor concentrations reached a mean peak of 33.7 ng/mL 2 hours following single-dose administration of TOBRADEX ST.

No data are available on the extent of systemic absorption of tobramycin from TOBRADEX ST ophthalmic suspension. Following multiple-dose (4 times a day for 2 days) bilateral ocular administration of TOBRADEX (tobramycin 0.3% and dexamethasone 0.1% ophthalmic suspension) in healthy male and female volunteers, peak plasma concentrations of dexamethasone were less than 1 ng/mL and occurred within 2 hours post dose across all subjects.

12.4 Microbiology

The antibiotic component (tobramycin) in the combination is included to provide action against susceptible bacteria. In vitrostudies have demonstrated that tobramycin is active against susceptible isolates of the following bacteria: Staphylococcus aureus(includes penicillin-resistant isolates), Staphylococcus epidermidis(includes penicillin-resistant isolates), Streptococci, including some Group A other beta-hemolytic species, some nonhemolytic species, and some Streptococcus pneumoniae.

Acinetobacter calcoaceticus, Enterobacter aerogenes, Escherichia coli, Haemophilus influenzae, Haemophilus aegypticus, Klebsiella pneumoniae, Moraxella lacunata, Morganella morganii, Neisseria perflava, Neisseria sicca, Proteus mirabilis, Proteus vulgaris, Pseudomonas aeruginosa.

In vitrobacterial studies demonstrate that in some cases bacteria resistant to gentamicin are susceptible to tobramycin.

13 NONCLINICAL TOXICOLOGY

13.1 Carcinogenesis, Mutagenesis, Impairment of Fertility

No studies have been conducted to evaluate the carcinogenic or mutagenic potential. There are no adequate and well-controlled studies in pregnant women. TOBRADEX ST ophthalmic suspension should be used during pregnancy only if the potential benefit justifies the potential risk to the fetus.

No impairment of fertility was noted in studies of subcutaneous tobramycin in rats at doses of 50 and 100 mg/kg/day (equivalent to human doses of 8 and 16 mg/kg/day, at least 2 orders of magnitude greater than the topical ocular dose).

16 HOW SUPPLIED/STORAGE AND HANDLING

TOBRADEX ST is supplied as a 2.5 mL or 5 mL suspension in a 4 mL or 8 mL natural polyethylene DROP-TAINER®bottle with a natural polyethylene dispenser tip and a pink polypropylene overcap. Tamper evidence is provided with a shrink band around the closure and neck area of the bottle.

2.5 mL | NDC 82667-011-00
5 mL | NDC 82667-011-05

Storage

Store at 2°C to 25°C (36°F to 77°F). Protect from light. After opening, TOBRADEX ST can be used until the expiration date on the bottle.

17 PATIENT COUNSELING INFORMATION

Storage and Handling

Instruct the patient to store the bottle upright and away from light. Shake well before using [see Dosage and Administration (2.1)and How Supplied/Storage and Handling (16)] .

Avoid Contamination

Instruct the patient not to touch dropper tip to any surface, as this may contaminate the contents [see Warnings and Precautions (5.9)] .

Contact Lens Wear

Advise the patient that contact lenses should not be worn during the use of this product [see Warnings and Precautions (5.10)] .

Ability to Drive and Use Machines

Advise the patient that vision may be temporarily blurred following dosing with TOBRADEX ST. Care should be exercised in operating machinery or driving a motor vehicle [see Warnings and Precautions (5.8)] .

Manufactured for: Harrow Eye, LLC™ Nashville, TN USA

PRINCIPAL DISPLAY PANEL

NDC 82667-011-05

TobraDex® ST

(tobramycin and dexamethasone ophthalmic suspension) 0.3%/0.05%

STERILE

5 mL

HARROW®